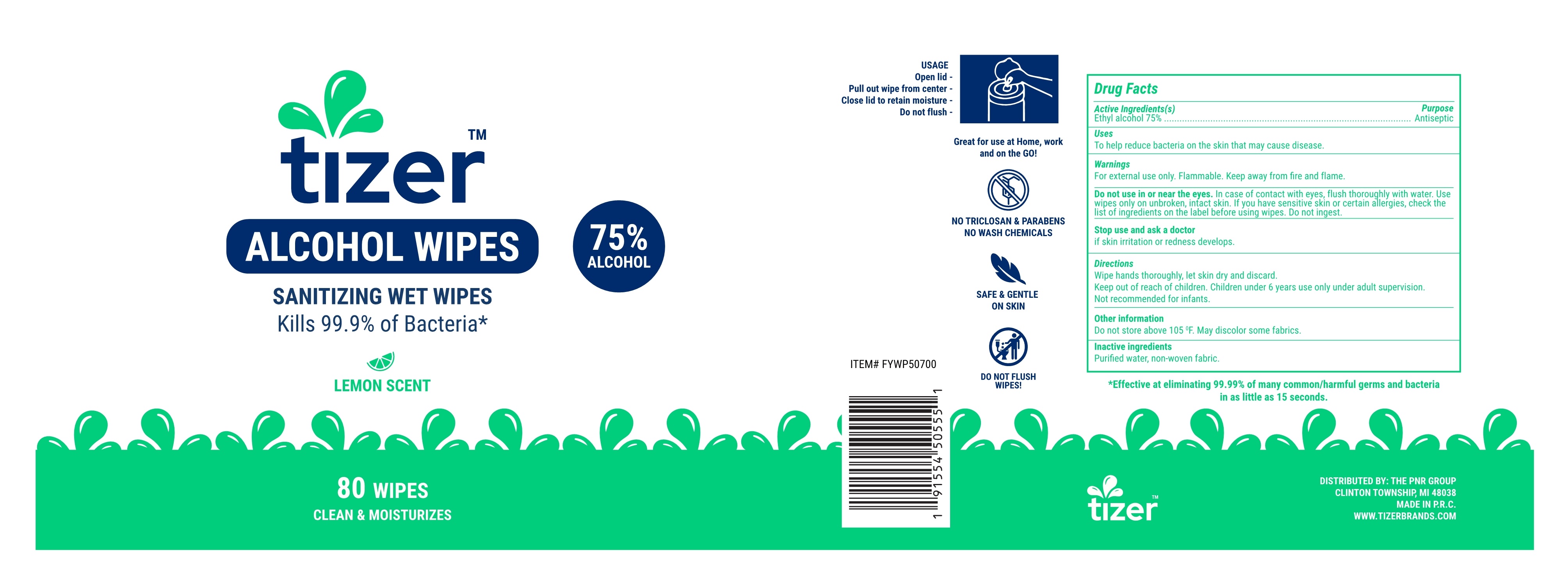 DRUG LABEL: ALCOHOL WIPES
NDC: 11749-080 | Form: CLOTH
Manufacturer: Pnr Group, LLC
Category: otc | Type: HUMAN OTC DRUG LABEL
Date: 20200816

ACTIVE INGREDIENTS: ALCOHOL 75 mL/100 g
INACTIVE INGREDIENTS: WATER

11749-080-80 ALCOHOL WIPES /ALCOHOL WIPES FuYang YangYang Health Technology Co. Ltd
.

Active Ingredient(s)

Alcohol 75% v/v. Purpose: Antiseptic

Purpose

Antiseptic, Alcohol Wet Wipes

Use

To help reduce bacteria on the skin that may cause disease.

Usage:

Open lid---Pull out wipe from center---Close lid to retain moisture---Do no flush.

Warnings

For external use only. Flammable. Keep away from fire and flame.

- Do not use in or near the eyes. In case of contact with eyes, flush thoroughly with water. Use wipes only on unbroken, intact skin. If you have sensitive skin or certain allergies, check the list of ingredients on the label before using wipes. Do not ingest.

When using this product keep out of eyes, ears, and mouth. In case of contact with eyes, rinse eyes thoroughly with water.
Stop use and ask a doctor if irritation or rash occurs. These may be signs of a serious condition.
Keep out of reach of children. If swallowed, get medical help or contact a Poison Control Center right away.

Stop use and ask a doctor. if skin irritation or redness develops.

Keep out of reach of children. If swallowed, get medical help or contact a Poison Control Center right away.

Directions

Wipes hands thoroughly, let skin dry and discard.

Keep out of children. Children under 6 years use only under adult supervision.

Not recommended for infants.

Other information

Do not store above 105℉. May discolor some fabrics.

Inactive ingredients

Water, Aloe vera, Citrus Scent.

SPL UNCLASSIFIED SECTION

ALCOHOL WIPES

SANITIZING WET WIPES

Kills 99.9% of Bacteria*

LEMON SCENT

75% ALCOHOL

80 WIPES

CLEAN & MOISTURIZES

Great for use at Home, work and on th GO!

NO TRICLOSAN & PARABENS NO WASH CHEMICALS

SAFE & GENTLE ON SKIN

DO NOT FLUSH WIPES!

Effective at eliminating 99.99% of many common/harmful germs and becteria in as little as 15 seconds.

Package Label - Principal Display Panel

80 Wipes NDC: 11749-080-80